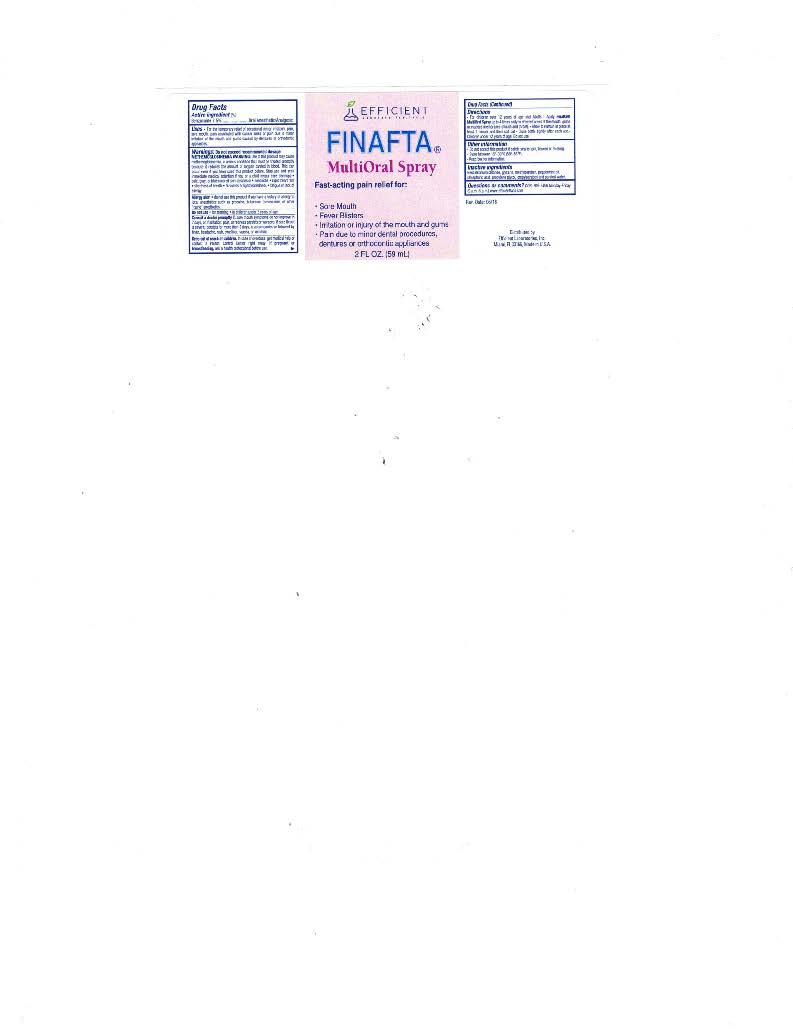 DRUG LABEL: Finafta

NDC: 65852-001 | Form: SPRAY
Manufacturer: Dextrum Laboratories Inc.
Category: otc | Type: HUMAN OTC DRUG LABEL
Date: 20250923

ACTIVE INGREDIENTS: BENZOCAINE 7.5 mg/100 mL
INACTIVE INGREDIENTS: BENZALKONIUM CHLORIDE; METHYLPARABEN; PEPPERMINT OIL; PHOSPHORIC ACID; PROPYLENE GLYCOL; PROPYLPARABEN; WATER; GLYCERIN

Finafta Multioral

Active Ingredients: (%) Purpose

Benzocaine USP 7.5% ................ Oral Anesthetic/Analgesic

Purpose

Oral Anesthetic/Analgesic

Warnings: Do not exceed recommended dosage

Methemoglobinemia warning:Use of this product may cause mthemoglobinemia, a serious condition that must be treated promptyly because it reduces the amount of oxygen carried in the blood. This can occur even if you have used this product before. Stop use and seek immediate medical attention if you or a child in your care develops:

- pale, gray, or blue colored skin (cyanosis)
- headache
- rapid heart rate
- shortness of breath
- dizziness or lightheadedness
- fatigue or lack of enegry

Allegry alert

do not use this product if you have a history of allergy to local anesthetics such as prcaine, butacaine, bezocaine, or other "caine" anesthetics.

Do not use

- for teething
- in children under 2 years of age

Consult a doctor promptly if:

sore mouth symptoms do not improve in 7 days, or if irritation, pain, or redness persists or worsens. If sore throat is sever, persists for more than 2 days, is accompanied or followed by fever, headache, rash, swelling, nausea, or vomiting.

Keep Out of reach of children.In case of accidental overdose, get medical help or contact a Poison
Control Center right away.

PREGNANCY OR BREAST FEEDING

If pregnant or breastfeeding, ask a health professional before use.

DIRECTIONS:

For children over 12 years of age and Adults
• Apply Finafta® MultiOral Spray up to 4 times daily to affected areas of the mouth, gums or mucus membranes (mouth and throat).

- Allow to remain in place at least 1 minute and then spit out.

• Close bottle tightly after each use.

- Children under 12 years of age: Do not use.

USES

For the temporary relief of occasional minor irritation, pain, sore mouth, pain associated with canker sores or pain due to minor irritation of the mouth and gums cause by dentures or othodontic applicances.

Inactive ingredients:

Benzalkonium chloride, glycerin, methylparaben, peppermint oil, phosphoric acid, propylene glycol, propylparaben and purified water.

QUESTIONS OR COMMENTS?
305-805-3456
Monday-Friday (9 a.m.- 5 p.m. EST)
www.efficientlabs.com